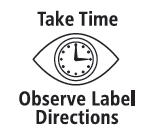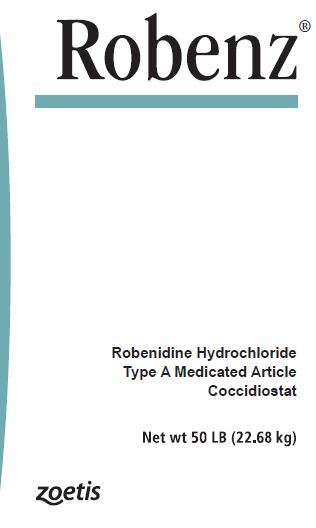 DRUG LABEL: Robenz
NDC: 54771-1128 | Form: POWDER
Manufacturer: Zoetis Inc.
Category: animal | Type: OTC TYPE A MEDICATED ARTICLE ANIMAL DRUG LABEL
Date: 20200408

ACTIVE INGREDIENTS: ROBENIDINE HYDROCHLORIDE 30 g/0.45 kg

Robenz®

Robenidine Hydrochloride
Type A Medicated Article
Coccidiostat

Active drug ingredient

Robenidine hydrochloride 30 grams per pound (6.6%) in a carrier suitable for incorporation in feed.

PURPOSE

For use in manufacturing medicated feeds only

Indications

Broiler chickens

As an aid in the prevention of coccidiosis caused by Eimeria mivati, E. brunetti, E. tenella, E. acervulina, E. maxima and E. necatrix in broiler chickens only.

Use directions

Mix 1 pound of Robenz® Type A Medicated Article in one ton of feed to provide 30 grams per ton (0.0033%) robenidine hydrochloride concentration in feed. Feed continuously as the sole ration.

Caution

Type C feeds containing Robenz robenidine hydrochloride must be fed within 50 days from the date of manufacture. Do not use this product in Type B or C medicated feeds containing bentonite

Warning

Do not feed to chickens producing eggs for food. Withdraw 5 days prior to slaughter.

Note

Manufacture of Type B and C feeds from this product requires a medicated feed mill license.

Labels for feeds containing Robenz must contain appropriate indications, limitations and warnings as well as required feed ingredient information.

Restricted Drug (California) - Use Only as Directed.

Not for human use.

Store below 25°C (77°F), excursions permitted to 37°C (99°F).

Approved by FDA under NADA # 048-486

zoetis
Manufactured by:
Zoetis LLC
Salisbury, MD 21801
Distributed by:
Zoetis Inc.
Kalamazoo, MI 49007
Product of Spain
40027288